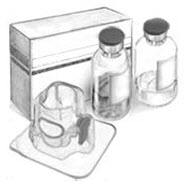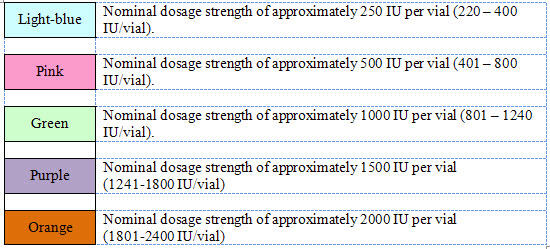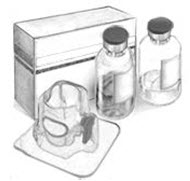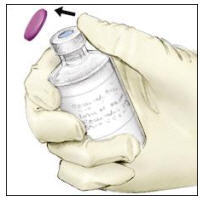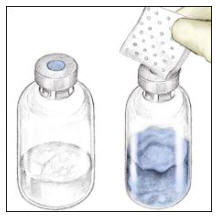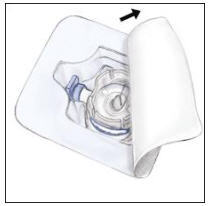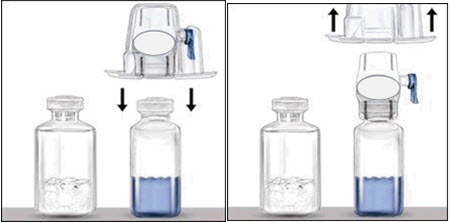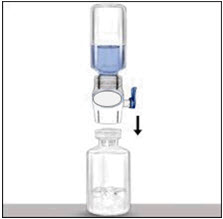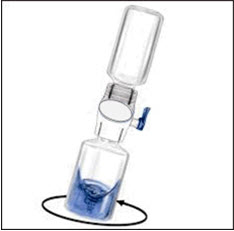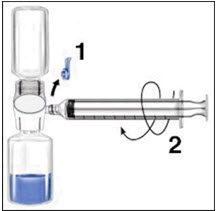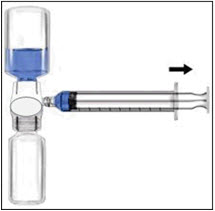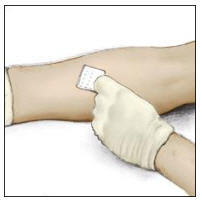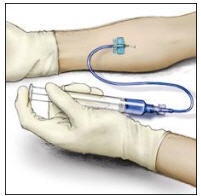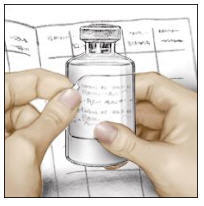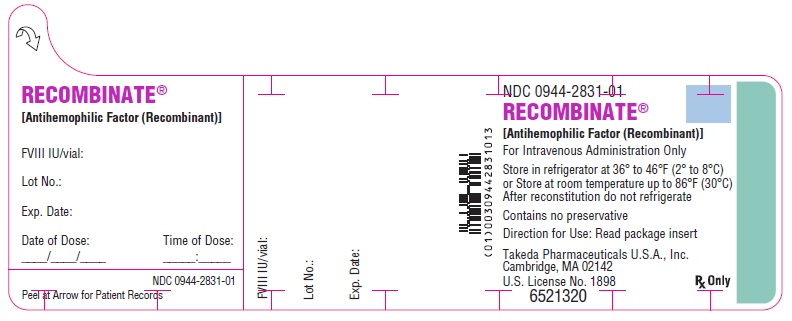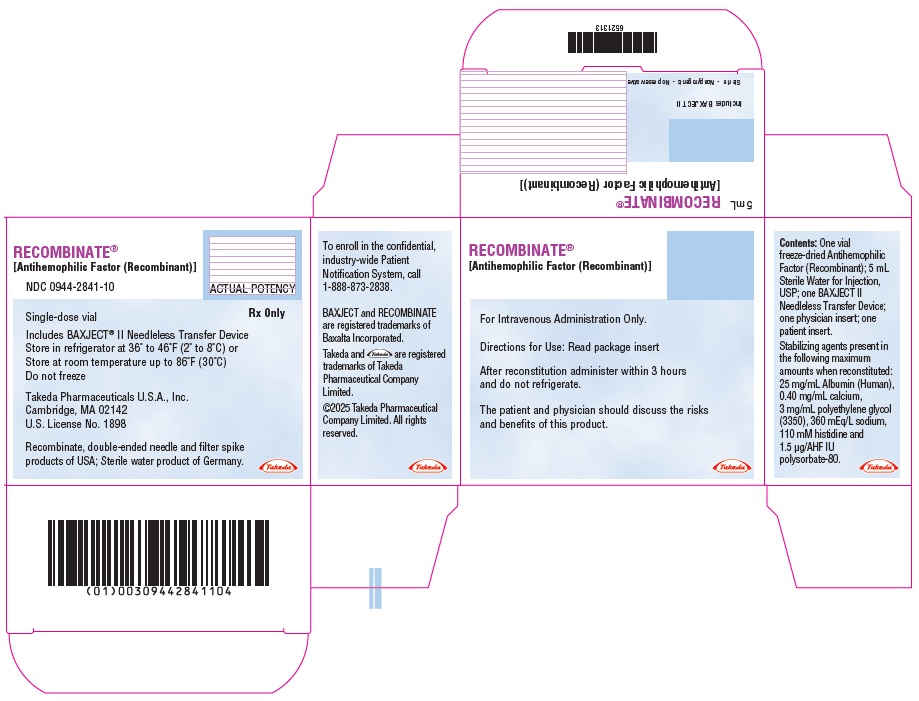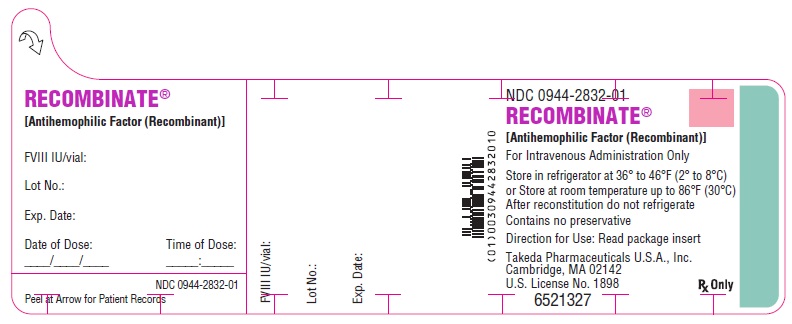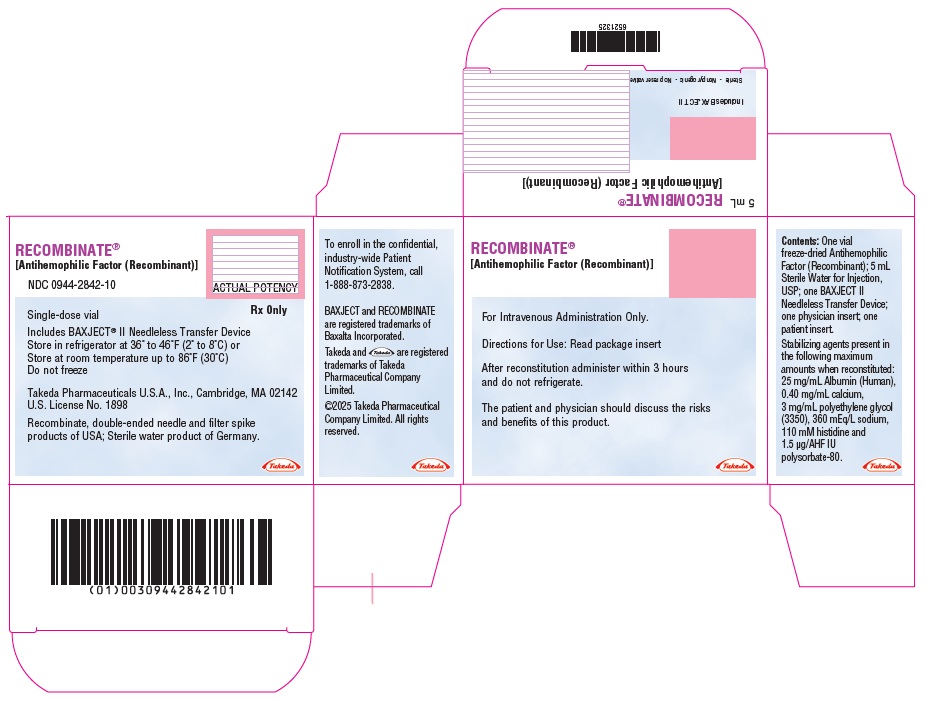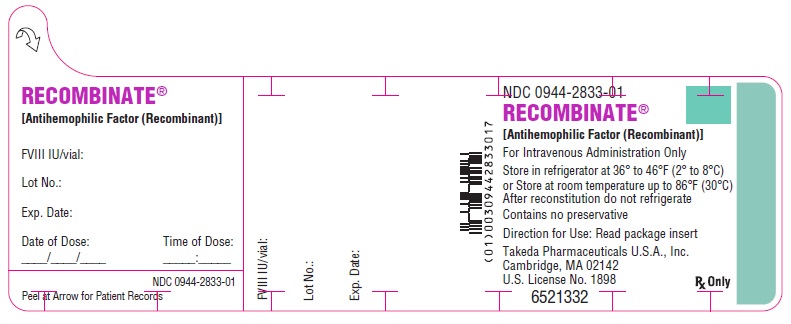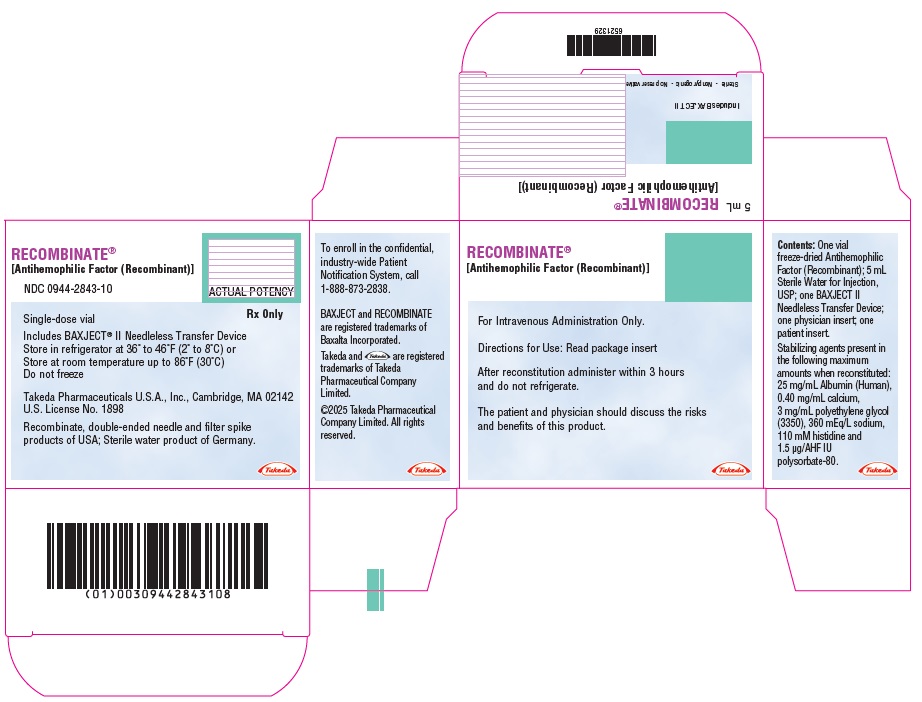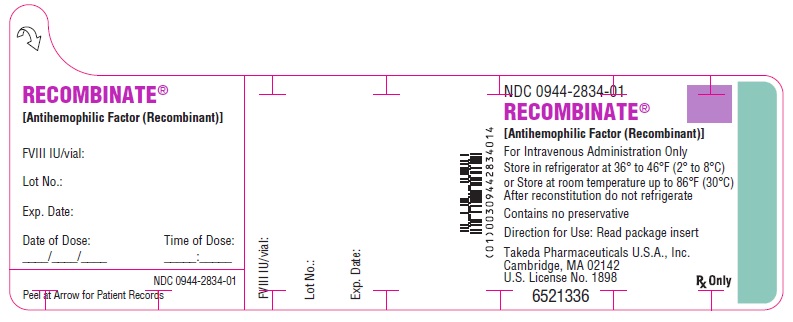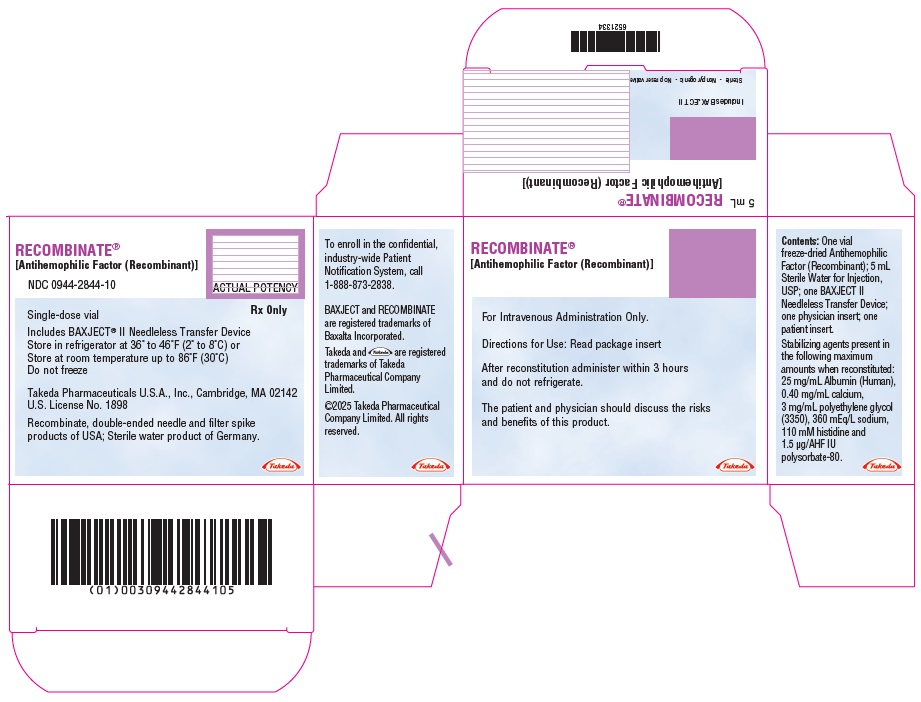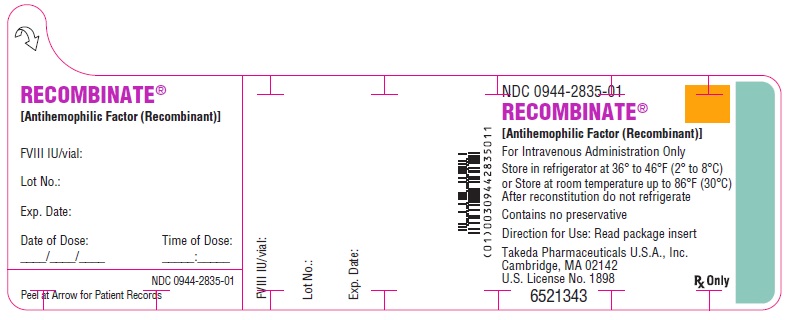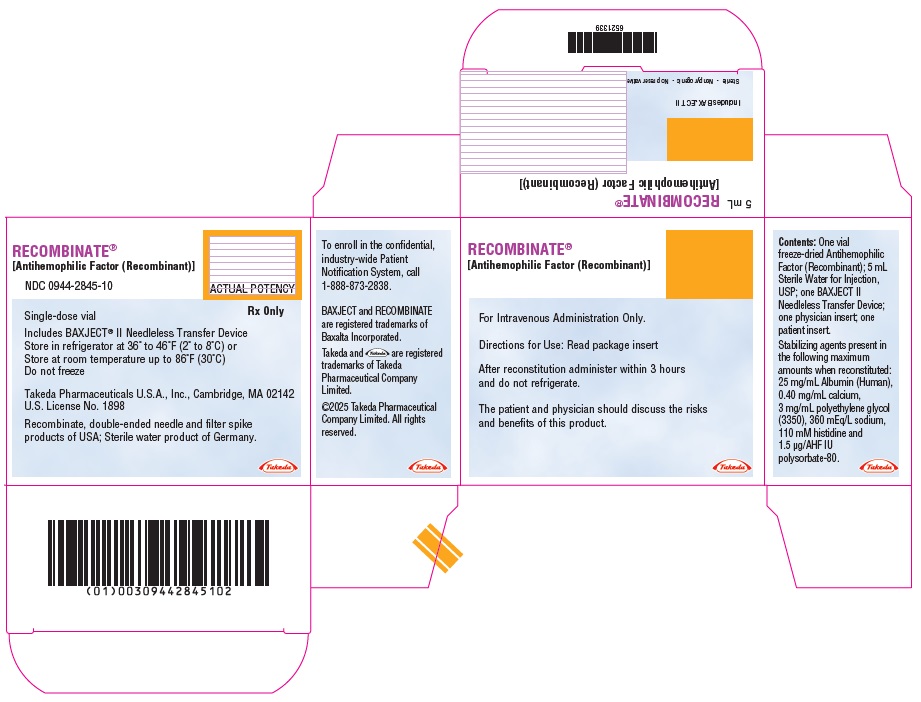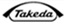 DRUG LABEL: RECOMBINATE
NDC: 0944-2841 | Form: KIT | Route: INTRAVENOUS
Manufacturer: Takeda Pharmaceuticals America, Inc.
Category: other | Type: PLASMA DERIVATIVE
Date: 20250403

ACTIVE INGREDIENTS: ANTIHEMOPHILIC FACTOR, HUMAN RECOMBINANT 250 [iU]/5 mL
INACTIVE INGREDIENTS: ALBUMIN HUMAN; CALCIUM CHLORIDE; POLYETHYLENE GLYCOL 3350; SODIUM CHLORIDE; HISTIDINE; POLYSORBATE 80; WATER 5 mL/5 mL

RECOMBINATE®
[Antihemophilic Factor (Recombinant)]

Lyophilized Powder for Reconstitution for injection

Reconstitute with 5 mL of Sterile Water for Injection using BAXJECT® II

DESCRIPTION

RECOMBINATE [Antihemophilic Factor (Recombinant)] is a glycoprotein synthesized by a genetically engineered Chinese Hamster Ovary (CHO) cell line. In culture, the CHO cell line secretes recombinant Factor VIII (rFVIII) into the cell culture medium. The rFVIII is purified from the culture medium utilizing a series of chromatography columns. A key step in the purification process is an immunoaffinity chromatography methodology in which a purification matrix, prepared by immobilization of a monoclonal antibody directed to Factor VIII, is utilized to selectively isolate the rFVIII in the medium. The synthesized rFVIII produced by the CHO cells has the same biological effects as human Factor VIII. Structurally the protein has a similar combination of heterogenous heavy and light chains as found in human Factor VIII.

RECOMBINATE is formulated as a sterile, nonpyrogenic, off-white to faint yellow, lyophilized powder preparation of concentrated recombinant Factor VIII for intravenous injection. RECOMBINATE is available in single-dose vials, which contain nominally 250, 500, 1000, 1500, and 2000 International Units per vial. When reconstituted with the appropriate volume of diluent, the product contains the following stabilizers in maximum amounts: For 5 mL reconstitution volume: 25 mg/mL Albumin (Human), 0.40 mg/mL calcium, 3 mg/mL polyethylene glycol (3350), 360 mEq/L sodium, 110 mM histidine, 1.5 µg/Factor VIII International Unit (IU) polysorbate-80. Recombinant Von Willebrand Factor (rVWF) is coexpressed with the rFVIII and helps to stabilize it. The final product contains not more than 2 ng rVWF/IU rFVIII, which will not have any clinically relevant effect in patients with von Willebrand's disease. The product contains no preservative.

Each vial of RECOMBINATE is labeled with the Factor VIII activity expressed in IU per vial. Biological potency is determined by an in vitro assay which is referenced to the World Health Organization (WHO) International Standard for Factor VIII:C Concentrate.

CLINICAL PHARMACOLOGY

Factor VIII is the specific clotting factor deficient in patients with hemophilia A (classical hemophilia). Hemophilia A is a genetic bleeding disorder characterized by hemorrhages, which may occur spontaneously or after minor trauma. The administration of RECOMBINATE provides an increase in plasma levels of Factor VIII and can temporarily correct the coagulation defect in these patients. Pharmacokinetic studies on sixty-nine (69) patients revealed the circulating mean half-life for RECOMBINATE to be 14.6 ± 4.9 hours (n=67), which was not statistically significantly different from plasma-derived HEMOFIL M, [Antihemophilic Factor (Human), Method M, Monoclonal Purified]. The mean half-life of HEMOFIL M was 14.7 ± 5.1 hours (n=61). The actual baseline recovery observed with RECOMBINATE was 123.9 ± 47.7 IU/dL (n=23), which is significantly higher than the actual HEMOFIL M baseline recovery of 101.7 ± 31.6 IU/dL (n=61). However, the calculated ratio of actual to expected recovery with RECOMBINATE (121.2 ± 48.9%) is not different on average from HEMOFIL M (123.4 ± 16.4%).

The clinical study of RECOMBINATE in previously treated patients (individuals with hemophilia A who had been treated with plasma derived Factor VIII) was based on observations made on a study group of 69 patients. These individuals received cumulative amounts of Factor VIII ranging from 20,914 to 1,383,063 IU over the 48 month study. Patients were given a total of 17,700 infusions totaling 28,090,769 IU RECOMBINATE.

These patients were successfully treated for bleeding episodes on a demand basis and also for the prevention of bleeds (prophylaxis). Spontaneous bleeding episodes successfully managed include hemarthroses, soft tissue and muscle bleeds. Management of hemostasis was also evaluated in surgeries. A total of 24 procedures on 13 patients were performed during this study. These included minor (e.g. tooth extraction) and major (e.g. bilateral osteotomies, thoracotomy and liver transplant) procedures. Hemostasis was maintained perioperatively and postoperatively with individualized Factor VIII replacement.

A study of RECOMBINATE in previously untreated patients was also performed as part of an ongoing study. The study group was comprised of seventy-nine (79)^1 patients, of whom seventy-six (76) had received at least one infusion of RECOMBINATE. To date, this cohort has been given 12,209 infusions totaling over 11,277,043 IU of RECOMBINATE. Hemostasis was appropriately managed in spontaneous bleeding episodes, intracranial hemorrhage and surgical procedures.

INDICATIONS AND USAGE

The use of RECOMBINATE [Antihemophilic Factor (Recombinant)] is indicated in hemophilia A (classical hemophilia) for the prevention and control of hemorrhagic episodes.^2 RECOMBINATE is also indicated in the perioperative management of patients with hemophilia A (classical hemophilia).

RECOMBINATE can be of therapeutic value in patients with acquired Factor VIII inhibitors not exceeding 10 Bethesda Units per mL.^3 In clinical studies with RECOMBINATE, patients with inhibitors who were entered into the previously treated patient trial and those previously untreated children who have developed inhibitor activity on study, showed clinical hemostatic response when the titer of inhibitor was less than 10 Bethesda Units per mL. However, in such uses, the dosage of RECOMBINATE should be controlled by frequent laboratory determinations of circulating Factor VIII levels as well as the clinical status of the patient.

RECOMBINATE is not indicated in von Willebrand's disease.

CONTRAINDICATIONS

RECOMBINATE is contraindicated in patients who have manifested life-threatening immediate hypersensitivity reactions, including anaphylaxis, to the product or its components, including bovine, mouse or hamster proteins.

WARNINGS

General

The clinical response to RECOMBINATE may vary. If bleeding is not controlled with the recommended dose, the plasma level of factor VIII should be determined and a sufficient dose of RECOMBINATE should be administered to achieve a satisfactory clinical response. If the patient's plasma factor VIII level fails to increase as expected or if bleeding is not controlled after the expected dose, the presence of an inhibitor (neutralizing antibodies) should be suspected and appropriate testing performed. (see PRECAUTIONS - Monitoring Laboratory Tests).

Anaphylaxis and Severe Hypersensitivity Reactions

Allergic type hypersensitivity reactions, including anaphylaxis, have been reported with RECOMBINATE and have been manifested as dizziness, pruritus, rash, urticaria, flushing, angioedema/face swelling, laryngeal edema, dyspnea, pallor, pyrexia, nausea, paresthesia, hypotension, and loss of consciousness. Discontinue RECOMBINATE if symptoms occur and seek immediate emergency treatment. RECOMBINATE contains trace amounts of bovine proteins, mouse immunoglobulin G (MuIgG), and hamster (CHO) proteins. Patients treated with this product may develop hypersensitivity to these non-human mammalian proteins.

Neutralizing Antibodies

Patients treated with antihemophilic factor (AHF) products should be carefully monitored for the development of factor VIII inhibitors by appropriate clinical observations and laboratory tests. Inhibitors have been reported following administration of RECOMBINATE predominantly in previously untreated and minimally treated patients. The risk of developing inhibitors is highest during the first 20 exposure days. If expected plasma factor VIII activity levels are not attained, or if bleeding is not controlled with an expected dose, an assay that measures factor VIII inhibitor concentration should be performed (see PRECAUTIONS - Monitoring Laboratory Tests).

PRECAUTIONS

General

Certain components used in the packaging of this product contain natural rubber latex.

Identification of the clotting defect as a Factor VIII deficiency is essential before the administration of RECOMBINATE [Antihemophilic Factor (Recombinant)] is initiated. No benefit may be expected from this product in treating other deficiencies.

Formation of Antibodies to Mouse, Hamster or Bovine Protein

As RECOMBINATE contains trace amounts of mouse protein (maximum of 0.1 ng/IU RECOMBINATE), hamster protein (maximum of 1.5 ng CHO protein/IU RECOMBINATE), and bovine protein (maximum of 1 ng BSA/IU RECOMBINATE), the remote possibility exists that patients treated with this product may develop hypersensitivity to these non-human mammalian proteins.

Information for Patients

The patient and physician should discuss the risks and benefits of this product.

Allergic type hypersensitivity reactions have been observed with RECOMBINATE. Patients should be informed of the early signs of hypersensitivity reactions including hives, generalized urticaria, tightness of the chest, wheezing, hypotension, symptoms of laryngeal edema, and anaphylaxis. Patients should be advised to discontinue use of the product and contact their physician if these symptoms occur. Additionally, patients should be informed that local tissue irritation may occur when infusing RECOMBINATE reconstituted with 5 mL sWFI.

Monitoring Laboratory Tests

- Monitor plasma factor VIII activity levels by the one-stage clotting assay to confirm the adequate factor VIII levels have been achieved and maintained, when clinically indicated. (see DOSAGE AND ADMINISTRATION).
- Monitor for development of factor VIII inhibitors. Perform assay to determine if factor VIII inhibitor is present if expected factor VIII activity plasma levels are not attained, or if bleeding is not controlled with the expected dose of RECOMBINATE. Use Bethesda Units (BU) to titer inhibitors.
  - If the inhibitor is less than 10 BU per mL, the administration of additional RECOMBINATE concentrate may neutralize the inhibitor, and may permit an appropriate hemostatic response.
  - Adequate hemostasis may not be achieved if inhibitor titers are above 10 BU per mL. The inhibitor titer may rise following RECOMBINATE infusion as a result of an anamnestic response to factor VIII. The treatment or prevention of bleeding in such patients requires the use of alternative therapeutic approaches and agents.

Carcinogenesis, Mutagenesis, Impairment of Fertility

RECOMBINATE was tested for mutagenicity at doses considerably exceeding plasma concentrations of Factor VIII in vitro and at doses up to ten times the expected maximum clinical dose in vivo, and did not cause reverse mutations, chromosomal aberrations, or an increase in micronuclei in bone marrow polychromatic erythrocytes. Long-term studies in animals have not been performed to evaluate carcinogenic potential.

Pediatric Use

RECOMBINATE is appropriate for use in children of all ages, including the newborn. Safety and efficacy studies have been performed in both previously treated (n=23) and previously untreated (n=75) children. (See CLINICAL PHARMACOLOGY and PRECAUTIONS).

Pregnancy

Animal reproduction studies have not been conducted with RECOMBINATE. The safety of RECOMBINATE for use in pregnant women has not been established. It is not known whether RECOMBINATE can cause fetal harm when administered to a pregnant woman or can affect reproductive capacity. Physicians should carefully consider the potential risks and benefits for each specific patient before prescribing RECOMBINATE. RECOMBINATE should be given to a pregnant woman only if clearly needed.

Nursing Mothers

It is not known whether this drug is excreted into human milk. Because many drugs are excreted into human milk, caution should be exercised if RECOMBINATE is administered to nursing mothers. RECOMBINATE should be given to nursing mothers only if clinically needed.

ADVERSE REACTIONS

Adverse Reactions from Clinical Trials

During controlled clinical studies with RECOMBINATE enrolling 210 subjects, the most commonly reported adverse drug reactions were chills, flushing, rash and epistaxis.

System Organ Class (SOC) | Preferred MedDRA Term | Number of Subjects | Percent of Evaluable Subjects [Number of evaluable subjects experiencing the event/total number of evaluable subjects [% relative to 210, the total number of unique subjects who received at least 1 infusion of RECOMBINATE].]
GASTROINTESTINAL DISORDERS | Nausea | 1 | 0.48
GENERAL DISORDERS AND ADMINISTRATION SITE CONDITIONS | Chills; Fatigue; Pyrexia | 3; 1; 1 | 1.43; 0.48; 0.48
INFECTIONS AND INFESTATIONS | Ear infections | 1 | 0.48
INVESTIGATIONS | Acoustic stimulation tests abnormal | 1 | 0.48
MUSCULOSKELETAL AND CONNECTIVE TISSUES DISORDERS | Pain in extremity | 1 | 0.48
NERVOUS SYSTEM DISORDERS | Dizziness; Tremors | 1; 1 | 0.48; 0.48
RESPIRATORY, THORACIC AND MEDIASTINAL DISORDERS | Pharyngolaryngeal pain | 1 | 0.48
SKIN AND SUBCUTANEOUS TISSUE DISORDERS | Hyperhidrosis; Pruritus; Rash; Rash maculopapular | 1; 1; 2; 1 | 0.48; 0.48; 0.95; 0.48
VASCULAR DISORDERS | Epistaxis; Flushing; Hematoma; Hypotension; Pallor; Peripheral coldness | 1 [One subject experienced 11 events of epistaxis.]; 2; 1; 1; 1; 1 | 0.48; 0.95; 0.48; 0.48; 0.48; 0.48

During the Previously Treated Patients (PTP) study, none of the 71 subjects developed de novo evidence of Factor VIII inhibitor. However, during the phase II/III portion of the study, 1 subject with a history of inhibitors exhibited inhibitor activity at 6 months (0.8 Bethesda Units [BU]), which resolved by 9 months. One other subject in this study had detectable Factor VIII inhibitor at baseline (1.26 BU) and exhibited an anamnestic response at 6 months (10.3 BU). During a prospective pharmaco-surveillance study of subjects who received batches of RECOMBINATE containing modestly increased Chinese Hamster Ovary (CHO) cell protein levels, none of the 34 treated subjects developed a Factor VIII inhibitor.

During the Previously Untreated Patients (PUP) study, 22 of the 73 evaluable subjects developed inhibitors to Factor VIII. Of these, 13 subjects displayed no detectable Factor VIII inhibitors at study exit.

Post-Marketing Adverse Reactions

In addition to the adverse reactions noted in clinical trials, the following adverse reactions have been reported in the post-marketing experience. These adverse reactions are listed by MedDRA (version 12.1) System Organ Class (SOC), then by MedDRA coding system Preferred Term in order of severity.

BLOOD AND LYMPHATIC SYSTEM DISORDERS: Factor VIII inhibition

CARDIAC DISORDERS: Tachycardia, Cyanosis

GASTROINTESTINAL DISORDERS: Vomiting, Abdominal pain

GENERAL DISORDERS AND ADMINISTRATION SITE CONDITIONS: Malaise, Injection site reactions, Chest pain, Chest discomfort

IMMUNE SYSTEM DISORDERS: Anaphylactic reaction, Hypersensitivity

NERVOUS SYSTEM DISORDERS: Loss of consciousness, Headache, Paresthesia

RESPIRATORY, THORACIC AND MEDIASTINAL DISORDERS: Dyspnea, Cough, Laryngeal edema

SKIN AND SUBCUTANEOUS TISSUE DISORDERS: Angioedema, Urticaria, Erythema

DOSAGE AND ADMINISTRATION

Each vial of RECOMBINATE is labeled with the Factor VIII activity expressed in IU per vial. This potency assignment is referenced to the World Health Organization International Standard for Factor VIII:C Concentrate and is evaluated by appropriate methodology to ensure accuracy of the results.

The expected in vivo peak increase in Factor VIII level expressed as IU/dL of plasma or % (percent) of normal can be estimated by multiplying the dose administered per kg body weight (IU/kg) by two. This calculation is based on the clinical findings of Abildgaard et al ^4 and is supported by the data generated by 419 clinical pharmacokinetic studies with RECOMBINATE in 67 patients over time. This pharmacokinetic data demonstrated a peak recovery point above the pre-infusion baseline of approximately 2.0 IU/dL per IU/kg body weight.

Examples (Assuming patient's baseline Factor VIII level is at <1%):

(1) A dose of 1750 IU RECOMBINATE administered to a 70 kg patient, i.e. 25 IU/kg (1750 IU/70 kg), should be expected to cause a peak post-infusion Factor VIII increase of 25 IU/kg x 2 (IU/dL)/(IU/kg) = 50 IU/dL (50% of normal).
(2) A peak level of 70% is required in a 40 kg child. In this situation, the dose would be 70 IU/dL/[2(IU/dL)/(IU/kg)] x 40 kg = 1400 IU.

Recommended Dosage Schedule

Physician supervision of the dosage is required. The following dosage schedule may be used as a guide.

Hemorrhage
Degree of hemorrhage | Required peak post-infusion Factor VIII activity in the blood (as % of normal or IU/dL plasma) | Frequency of Infusion
Early hemarthrosis or muscle bleed or oral bleed | 20-40 | Begin infusion every 12 to 24 hours for one-three days until the bleeding episode is resolved (as indicated by pain), or healing is achieved.
More extensive hemarthrosis, muscle bleed, or hematoma | 30-60 | Repeat infusion every 12 to 24 hours for (usually) three days or more until pain and disability are resolved.
Life threatening bleeds such as head injury, throat bleed, severe abdominal pain | 60-100 | Repeat infusion every 8 to 24 hours until threat is resolved.
Surgery
Type of operation
Minor surgery, including tooth extraction | 60-80 | A single infusion plus oral antifibrinolytic therapy within one hour is sufficient in approximately 70% of cases.
Major surgery | 80-100 (pre- and post-operative) | Repeat infusion every 8 to 24 hours depending on state of healing.

If bleeding is not controlled with the recommended dose, the plasma level of Factor VIII should be determined and a sufficient dose of RECOMBINATE should be administered to achieve a satisfactory clinical response.

The careful control of the substitution therapy is especially important in cases of major surgery or life threatening hemorrhages. In presence of a low titer inhibitor, doses larger than those recommended may be necessary as per standard care.

Although dosage can be estimated by the calculations above, it is strongly recommended that whenever possible, appropriate laboratory tests including serial Factor VIII assays be performed on the patient's plasma at suitable intervals to assure that adequate Factor VIII levels have been reached and are maintained.

Patients should be evaluated for the development of Factor VIII inhibitors, if the expected plasma Factor VIII activity levels are not attained, or if bleeding is not controlled with an appropriate dose.

Reconstitution: Use Aseptic Technique

1. Bring RECOMBINATE (dry factor concentrate) and Sterile Water for Injection, USP, (diluent) to room temperature.
2. Remove caps from concentrate and diluent vials.
3. Cleanse stoppers with germicidal solution and allow to dry prior to use. Place vials on a flat surface.
4. Open the BAXJECT II device package by peeling away the lid, without touching the inside. Do not remove the device from the package.
5. Turn the package over. Press straight down to fully insert the clear plastic spike through the diluent vial stopper.
6. Grip the BAXJECT II package at its edge and pull the package off the device. Do not remove the blue cap from the BAXJECT II device. Do not touch the exposed white plastic spike.
7. Turn the system over, so that the diluent vial is on top. Quickly insert the white plastic spike fully into the RECOMBINATE vial stopper by pushing straight down. The vacuum will draw the diluent into the RECOMBINATE vial.
8. Swirl gently until RECOMBINATE is completely dissolved. After reconstitution, the solution should be colorless to faint yellow, and substantially free from foreign particles.

NOTE: Do not refrigerate after reconstitution. (see Administration)

Administration: Use Aseptic Technique

RECOMBINATE is administered by intravenous (IV) injection after reconstitution.

Administer at room temperature.
RECOMBINATE should be administered not more than 3 hours after reconstitution.

Intravenous Syringe Injection

Parenteral drug products should be inspected for particulate matter and discoloration prior to administration, whenever solution and container permit. The solution should be colorless to faint yellow in appearance. If not, do not use the solution and notify Takeda Pharmaceuticals U.S.A., Inc. immediately.

Plastic syringes are recommended for use with this product since proteins such as RECOMBINATE tend to stick to the surface of glass syringes.

1. Remove the blue cap from the BAXJECT II device. Connect the syringe to the BAXJECT II device. DO NOT INJECT AIR.
2. Turn over the connected vials so that the RECOMBINATE vial is on top. Draw the factor concentrate into the syringe by pulling the plunger back slowly.
3. Disconnect the syringe; attach a suitable needle and inject intravenously as instructed (see Rate of Administration)
4. If a patient is to receive more than one vial of RECOMBINATE, the contents of multiple vials may be drawn into the same syringe. Please note that the BAXJECT II device is intended for use with a single vial of RECOMBINATE and Sterile Water for Injection only, therefore reconstituting and withdrawing a second vial into the syringe requires a second BAXJECT II device.

Rate of Administration

The rate of administration should be a rate that ensures the comfort of the patient. Preparations of RECOMBINATE can be administered at a rate of up to 5 mL per minute when reconstituted with 5 mL of sWFI.

The pulse rate should be determined before and during administration of RECOMBINATE. Should a significant increase in pulse rate occur, reducing the rate of administration or temporarily halting the injection usually allows the symptoms to disappear promptly.

HOW SUPPLIED

RECOMBINATE is available in five different strengths in single-dose vials. The strength is designated on the outer box and on the vial label using the following color codes:

Color Code | Dosage Strength | RECOMBINATE Supplied with 5 mL sWFI
Light blue bar | 220-400 IU per vial | NDC 0944-2841-10
Pink bar | 401-800 IU per vial | NDC 0944-2842-10
Green bar | 801-1240 IU per vial | NDC 0944-2843-10
Purple bar | 1241-1800 IU per vial | NDC 0944-2844-10
Orange bar | 1801-2400 IU per vial | NDC 0944-2845-10

RECOMBINATE is packaged with 5 mL of Sterile Water for Injection, USP, a BAXJECT II Needleless Transfer Device, one physician insert and one patient insert.

Storage

RECOMBINATE can be refrigerated [2° - 8°C (36° - 46°F)] or stored at room temperature, not to exceed 30°C (86°F). Avoid freezing to prevent damage to the diluent vial. Do not use beyond the expiration date printed on the box.

CLINICAL STUDIES

Over the investigational period of the original safety and efficacy study of RECOMBINATE, none of the 69 subjects without an inhibitor at entry into the study, developed an inhibitor. In the previously untreated patient group there were 73 eligible subjects with Factor VIII levels less than or equal to 2% who received at least one RECOMBINATE treatment (median days 100, range 3-821) and who were tested for an inhibitor after treatment with RECOMBINATE. Of this group, 23 individuals (32%) developed a detectable inhibitor (median days on treatment at time of detection 10, range 3-69) and of these, 8 subjects (11%) showed a titer greater than 10 B.U.

REFERENCES

1. Bray GL, Gomperts ED, Courter S, Gruppo R, et al: A Multicenter Study of Recombinant Factor VIII (Recombinate): Safety, Efficacy, and Inhibitor Risk in Previously Untreated Patients with Hemophilia A Blood 83:2428-2435, 1994
2. White GC, McMillan CW, Kingdon HS, et al: Use of recombinant antihemophilic factor in the treatment of two patients with classic hemophilia. New Eng J Med 320:166-170, 1989
3. Kessler CM: An Introduction to Factor VIII Inhibitors: The Detection and Quantitation. Am J Med 91 (Suppl 5A):1S-5S, 1991
4. Abildgaard CF, Simone JV, Corrigan JJ, et al: Treatment of hemophilia with glycine-precipitated Factor VIII. New Eng J Med 275:471-475, 1966

To enroll in the confidential, industry-wide Patient Notification System, call 1-888-873-2838.

Takeda Pharmaceuticals U.S.A., Inc.
Cambridge, MA 02142
U.S. License No. 1898

BAXJECT and RECOMBINATE are registered trademarks of Baxalta Incorporated.

Takeda and are registered trademarks of Takeda Pharmaceutical Company Limited.

©2025 Takeda Pharmaceutical Company Limited. All rights reserved.

Revised: 3/2025

Patient Information RECOMBINATE® [Antihemophilic Factor (Recombinant)]

This leaflet summarizes important information about RECOMBINATE. Please read it carefully before using this medicine. This information does not take the place of talking with your healthcare provider, and it does not include all of the important information about RECOMBINATE. If you have any questions after reading this, ask your healthcare provider.

Do not attempt to self-infuse unless you have been taught how by your doctor or hemophilia center.

What is RECOMBINATE [Antihemophilic Factor (Recombinant)]?

RECOMBINATE is a medicine used to replace a clotting factor (Factor VIII or antihemophilic factor) that is missing in people with hemophilia A (also called "classic" hemophilia). Hemophilia A is an inherited bleeding disorder that prevents blood from clotting normally.

RECOMBINATE is used to prevent and control bleeding in people with hemophilia A.

RECOMBINATE is not used to treat von Willebrand's Disease.

Who should not use RECOMBINATE [Antihemophilic Factor (Recombinant)]?

You should not use RECOMBINATE if you

- are allergic to mouse, hamster or bovine proteins.
- are allergic to any ingredients in RECOMBINATE (such as calcium, histidine, human albumin, polyethylene glycol, polysorbate-80 and sodium).

Tell your healthcare provider if you are pregnant or breast-feeding because RECOMBINATE may not be right for you.

How should I use RECOMBINATE [Antihemophilic Factor (Recombinant)]?

RECOMBINATE is given directly into the blood stream.

You may infuse RECOMBINATE at a hemophilia treatment center, at your healthcare provider's office or in your home. You should be trained on how to do infusions by your hemophilia treatment center or healthcare provider. Many people with hemophilia A learn to infuse their RECOMBINATE by themselves or with the help of a family member.

You must carefully follow your doctor's or other healthcare provider's instructions regarding the dose and schedule for infusing RECOMBINATE so that your treatment will work best for you.

Your healthcare provider will tell you how much RECOMBINATE to use based on your weight, the severity of your hemophilia A, and where you are bleeding.

You may have to have blood tests done after getting RECOMBINATE to be sure that your blood level of Factor VIII is high enough to clot your blood.

Call your healthcare provider right away if your bleeding does not stop after taking RECOMBINATE.

What should I tell my healthcare provider before I use RECOMBINATE [Antihemophilic Factor (Recombinant)]?

You should tell your healthcare provider if you

- have or have had any medical problems.
- take any medicines, including non-prescription medicines, dietary supplements and herbal remedies.
- have any allergies, including allergies to mouse, hamster or bovine proteins.
- are nursing.
- are pregnant or planning to become pregnant.
- have been told that you have inhibitors to Factor VIII (because Factor VIII may not work for you).

What are the possible side effects of RECOMBINATE [Antihemophilic Factor (Recombinant)]?

You could have an allergic reaction to RECOMBINATE.

Call your healthcare provider right away and stop treatment if you get a:

- Rash or hives
- itching
- tightness of the throat
- chest pain or tightness
- difficulty breathing
- light-headed, dizziness
- fainting

The most common side effects are chills, flushing, rash and nose bleeds. These are not all possible side effects with RECOMBINATE. You can ask your healthcare provider for information that is written for healthcare professionals. Tell your doctor about any side effect that bothers you or that does not go away.

What are the RECOMBINATE [Antihemophilic Factor (Recombinant)] dosage strengths?

RECOMBINATE comes in five different dosage strengths. The actual strength will be imprinted on the label and on the box. The five different strengths are coded, as follows:

Always check the potency printed on the label to make sure you are using the strength prescribed by your doctor. Always check the expiration date printed on the box. You should not use the product after the expiration date printed on the box.

How do I store RECOMBINATE [Antihemophilic Factor (Recombinant)]?

RECOMBINATE vials containing powdered product (without sterile diluent added) should be stored in a refrigerator (2° to 8°C [36° to 46°F]) or at room temperature (up to 30°C [86°F]).

If you choose to store RECOMBINATE at room temperature:

- it should remain at room temperature until infused.
- do not put room temperature product back in the refrigerator.

Store vials in their original box and protect them from extreme exposure to light.

Do not freeze.

Reconstituted product (after mixing dry product with wet diluent) must be used within 3 hours and cannot be stored or refrigerated. Any RECOMBINATE left in the vial at the end of your infusion should be discarded.

What else should I know about RECOMBINATE [Antihemophilic Factor (Recombinant)] and hemophilia A?

Your body may form inhibitors to Factor VIII. An inhibitor is part of the body's normal defense system. If you form inhibitors, it may stop RECOMBINATE from working properly. Call your healthcare provider right away if your bleeding does not stop after taking RECOMBINATE. Consult with your healthcare provider to make sure you are carefully monitored with blood tests for the development of inhibitors to Factor VIII.

Resources at Takeda available to the patients:

Contact Takeda for more product information: 1-877-TAKEDA-7 (1-877-825-3327).

INSTRUCTIONS FOR USE RECOMBINATE® [Antihemophilic Factor (Recombinant)] (For intravenous use only)

Do not attempt to do an infusion to yourself unless you have been taught how by your doctor or hemophilia center.

1. In a quiet place, prepare a clean flat surface and gather all the materials you will need for the infusion. Check the expiration date, and let the vial with the RECOMBINATE concentrate and the Sterile Water for Injection, USP (diluent) warm up to room temperature. Wash your hands and put on clean exam gloves. If infusing yourself at home, the use of gloves is optional.

2. Remove caps from the RECOMBINATE concentrate and diluent vials to expose the centers of the rubber stoppers.

3. Disinfect the stoppers with an alcohol swab (or other suitable solution suggested by your doctor or hemophilia center) by rubbing the stoppers firmly for several seconds, and allow to dry prior to use. Place the vials on a flat surface.

4. Open the BAXJECT® II device package by peeling away the lid, without touching the inside of the package. Do not remove the BAXJECT II device from the package.

5. Turn the package with the BAXJECT II device upside down, and place it over the top of the diluent vial. Fully insert the clear plastic spike of the device into the center of the diluent vial's stopper by pushing straight down. Grip the package at its edge and lift it off the device. Be careful not to touch the white plastic spike. Do not remove the blue cap from the BAXJECT II device.
The diluent vial now has the BAXJECT II device connected to it and is ready to be connected to the RECOMBINATE vial.

6. To connect the diluent vial to the RECOMBINATE vial, turn the diluent vial over and place it on top of the vial containing RECOMBINATE concentrate. Fully insert the white plastic spike into the RECOMBINATE vial's stopper by pushing straight down. Diluent will flow into the RECOMBINATE vial. This should be done right away to keep the liquid free of germs.

7. Swirl the connected vials gently and continuously until the RECOMBINATE is completely dissolved. Do not shake. The RECOMBINATE solution should be colorless to light-yellow in appearance. If not, do not use it and notify Takeda Pharmaceuticals U.S.A., Inc. immediately.

8. Take off the blue cap from the BAXJECT II device and connect the syringe. BE CAREFUL TO NOT INJECT AIR.

9. Turn over the connected vials so that the RECOMBINATE vial is on top. Draw the RECOMBINATE solution into the syringe by pulling back the plunger slowly. Disconnect the syringe from the vials. Attach the infusion needle to the syringe using a winged (butterfly) infusion set, if available. Point the needle up and remove any air bubbles by gently tapping the syringe with your finger and slowly and carefully pushing air out of the syringe and needle.

If you are using more than one vial of RECOMBINATE, the contents of more than one vial may be drawn into the same syringe. However, you will need a separate diluent and BAXJECT II device to mix each additional vial of RECOMBINATE.

10. Apply a tourniquet, and get the injection site ready by wiping the skin well with an alcohol swab (or other suitable solution suggested by your doctor or hemophilia center).

11. Insert the needle into the vein, and remove the tourniquet. Slowly infuse the RECOMBINATE. Do not infuse any faster than 5 mL per minute for RECOMBINATE dissolved with 5 mL of sWFI. Redness of the skin or irritation may be seen when infusing RECOMBINATE dissolved with 5 mL diluent.

12. Take the needle out of the vein and use sterile gauze to put pressure on the infusion site for several minutes.
Do not recap the needle. Place it with the used syringe in a hard-walled Sharps container for proper disposal.

13. Remove the peel-off label from the RECOMBINATE vial and place it in your logbook. Clean any spilled blood with a freshly prepared mixture of 1 part bleach and 9 parts water, soap and water, or any household disinfecting solution.

14. Dispose of the used vials and BAXJECT II system in your hard-walled Sharps container, without taking them apart. Do not dispose of these supplies in ordinary household trash.

Important: Contact your doctor or local Hemophilia Treatment Center if you experience any problems.

Takeda Pharmaceuticals U.S.A., Inc.
Cambridge, MA 02142
U.S. License No. 1898

BAXJECT and RECOMBINATE are registered trademarks of Baxalta Incorporated.

Takeda and are registered trademarks of Takeda Pharmaceutical Company Limited.

©2025 Takeda Pharmaceutical Company Limited. All rights reserved.

Revised: 3/2025

PRINCIPAL DISPLAY PANEL - 10 mL Vial Label - 250 IU

NDC 0944-2831-01

RECOMBINATE®

[Antihemophilic Factor (Recombinant)]

For Intravenous Administration Only

Store in refrigerator at 36° to 46°F (2° to 8°C)
or Store at room temperature up to 86°F (30°C)
After reconstitution do not refrigerate

Contains no preservative

Direction for Use: Read package insert

Takeda Pharmaceuticals U.S.A., Inc.
Cambridge, MA 02142
U.S. License No. 1898

Rx Only

6521320

PRINCIPAL DISPLAY PANEL - Kit Carton - 250 IU

RECOMBINATE®
[Antihemophilic Factor (Recombinant)]

NDC 0944-2841-10

ACTUAL POTENCY

Rx Only

Single-dose vial

Includes BAXJECT® II Needleless Transfer Device
Store in refrigerator at 36° to 46°F (2° to 8°C) or
Store at room temperature up to 86°F (30°C)
Do not freeze

Takeda Pharmaceuticals U.S.A., Inc.
Cambridge, MA 02142
U.S. License No. 1898

Recombinate, double-ended needle and filter spike
products of USA; Sterile water product of Germany.

Takeda

PRINCIPAL DISPLAY PANEL - 10 mL Vial Label - 500 IU

NDC 0944-2832-01

RECOMBINATE®

[Antihemophilic Factor (Recombinant)]

For Intravenous Administration Only

Store in refrigerator at 36° to 46°F (2° to 8°C)
or Store at room temperature up to 86°F (30°C)
After reconstitution do not refrigerate

Contains no preservative

Direction for Use: Read package insert

Takeda Pharmaceuticals U.S.A., Inc.
Cambridge, MA 02142
U.S. License No. 1898

Rx Only

6521327

PRINCIPAL DISPLAY PANEL - Kit Carton - 500 IU

RECOMBINATE®
[Antihemophilic Factor (Recombinant)]

NDC 0944-2842-10

ACTUAL POTENCY

Rx Only

Single-dose vial

Includes BAXJECT® II Needleless Transfer Device
Store in refrigerator at 36° to 46°F (2° to 8°C) or
Store at room temperature up to 86°F (30°C)
Do not freeze

Takeda Pharmaceuticals U.S.A., Inc., Cambridge, MA 02142
U.S. License No. 1898

Recombinate, double-ended needle and filter spike
products of USA; Sterile water product of Germany.

Takeda

PRINCIPAL DISPLAY PANEL - 10 mL Vial Label - 1000 IU

NDC 0944-2833-01

RECOMBINATE®

[Antihemophilic Factor (Recombinant)]

For Intravenous Administration Only

Store in refrigerator at 36° to 46°F (2° to 8°C)
or Store at room temperature up to 86°F (30°C)
After reconstitution do not refrigerate

Contains no preservative

Direction for Use: Read package insert

Takeda Pharmaceuticals U.S.A., Inc.
Cambridge, MA 02142
U.S. License No. 1898

Rx Only

6521332

PRINCIPAL DISPLAY PANEL - Kit Carton - 1000 IU

RECOMBINATE®
[Antihemophilic Factor (Recombinant)]

NDC 0944-2843-10

ACTUAL POTENCY

Rx Only

Single-dose vial

Includes BAXJECT® II Needleless Transfer Device
Store in refrigerator at 36° to 46°F (2° to 8°C) or
Store at room temperature up to 86°F (30°C)
Do not freeze

Takeda Pharmaceuticals U.S.A., Inc., Cambridge, MA 02142
U.S. License No. 1898

Recombinate, double-ended needle and filter spike
products of USA; Sterile water product of Germany.

Takeda

PRINCIPAL DISPLAY PANEL - 10 mL Vial Label - 1500 IU

NDC 0944-2834-01

RECOMBINATE®

[Antihemophilic Factor (Recombinant)]

For Intravenous Administration Only

Store in refrigerator at 36° to 46°F (2° to 8°C)
or Store at room temperature up to 86°F (30°C)
After reconstitution do not refrigerate

Contains no preservative

Direction for Use: Read package insert

Takeda Pharmaceuticals U.S.A., Inc.
Cambridge, MA 02142
U.S. License No. 1898

Rx Only

6521336

PRINCIPAL DISPLAY PANEL - Kit Carton - 1500 IU

RECOMBINATE®
[Antihemophilic Factor (Recombinant)]

NDC 0944-2844-10

ACTUAL POTENCY

Rx Only

Single-dose vial

Includes BAXJECT® II Needleless Transfer Device
Store in refrigerator at 36° to 46°F (2° to 8°C) or
Store at room temperature up to 86°F (30°C)
Do not freeze

Takeda Pharmaceuticals U.S.A., Inc., Cambridge, MA 02142
U.S. License No. 1898

Recombinate, double-ended needle and filter spike
products of USA; Sterile water product of Germany.

Takeda

PRINCIPAL DISPLAY PANEL - 10 mL Vial Label - 2000 IU

NDC 0944-2835-01

RECOMBINATE®

[Antihemophilic Factor (Recombinant)]

For Intravenous Administration Only

Store in refrigerator at 36° to 46°F (2° to 8°C)
or Store at room temperature up to 86°F (30°C)
After reconstitution do not refrigerate

Contains no preservative

Direction for Use: Read package insert

Takeda Pharmaceuticals U.S.A., Inc.
Cambridge, MA 02142
U.S. License No. 1898

Rx Only

6521343

PRINCIPAL DISPLAY PANEL - Kit Carton - 2000 IU

RECOMBINATE®
[Antihemophilic Factor (Recombinant)]

NDC 0944-2845-10

ACTUAL POTENCY

Rx Only

Single-dose vial

Includes BAXJECT® II Needleless Transfer Device
Store in refrigerator at 36° to 46°F (2° to 8°C) or
Store at room temperature up to 86°F (30°C)
Do not freeze

Takeda Pharmaceuticals U.S.A., Inc., Cambridge, MA 02142
U.S. License No. 1898

Recombinate, double-ended needle and filter spike
products of USA; Sterile water product of Germany.

Takeda